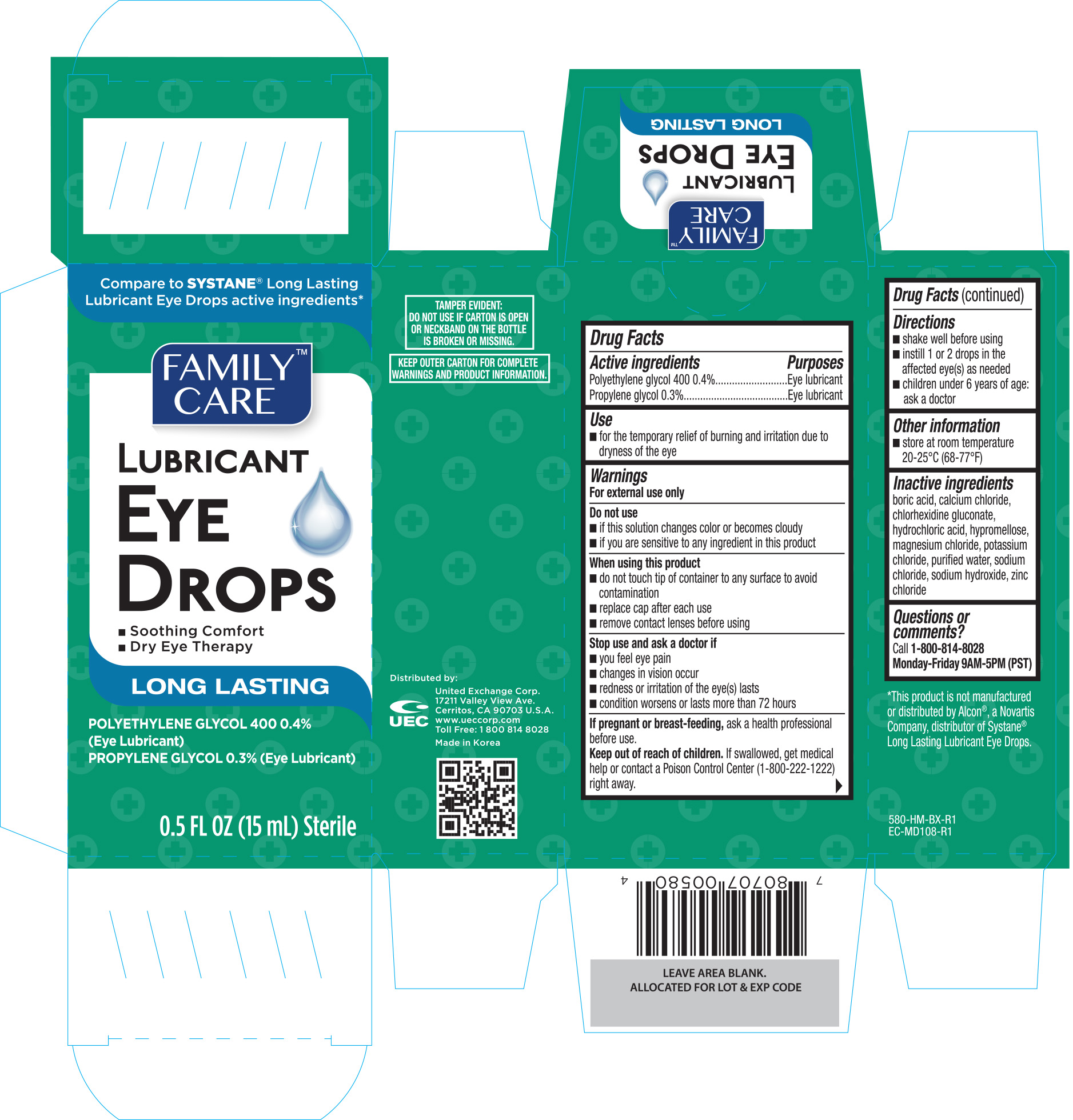 DRUG LABEL: Family Care Lubricant Eye
NDC: 65923-580 | Form: SOLUTION/ DROPS
Manufacturer: United Exchange Corp.
Category: otc | Type: HUMAN OTC DRUG LABEL
Date: 20170523

ACTIVE INGREDIENTS: POLYETHYLENE GLYCOL 400 4 mg/1 mL; PROPYLENE GLYCOL 3 mg/1 mL
INACTIVE INGREDIENTS: BORIC ACID; CALCIUM CHLORIDE; CHLORHEXIDINE GLUCONATE; HYDROCHLORIC ACID; HYPROMELLOSE, UNSPECIFIED; MAGNESIUM CHLORIDE; POTASSIUM CHLORIDE; WATER; SODIUM CHLORIDE; SODIUM HYDROXIDE; ZINC CHLORIDE

Active ingredients Purpose

Polyethylene glycol 400 0.4%...............................Eye lubricant

Propylene glycol 0.3%.........................................Eye lubricant

Use

- for the temporary relief of burning and irritation due to dryness of the eye

Warnings

For external use only

Do not use

- if this solution changes color or becomes cloudy
- if you are sensitive to any ingredient in this product

When using this product

- do not touch tip of container to any surface to avoid contamination
- replace cap after each use
- remove contact lense before using

Stop use and ask a doctor if

- you feel eye pain
- changes in vision occur
- redness or irritation of the eye(s) lasts
- condition worsens or lasts more than 72 hours

PREGNANCY OR BREAST FEEDING

If pregnant or breast-feeding, ask a health professional before use.

Keep out of reach of children. If swallowed, get medical help or contact a Poison Control Center (1-800-222-1222) right away.

Directions

- shake well before using
- instill 1 or 2 drops in the affected eye(s) as needed
- children under 6 years of age: ask a doctor

Other information

- store at room temperature 20-25°C (68-77°F)

Inactive ingredients

boric acid, calcium chloride, chlorhexidine gluconate, hydrochloric acid, hypromellose, magnesium chloride, potassium chloride, purified water,

sodium chloride, sodium hydroxide, zinc chloride

DOSAGE AND ADMINISTRATION

Distributed by:

United Exchange Corp.

17211 Valley View Ave.

Cerritos, CA 90703 U.S.A.

www.ueccorp.com

Made in Korea